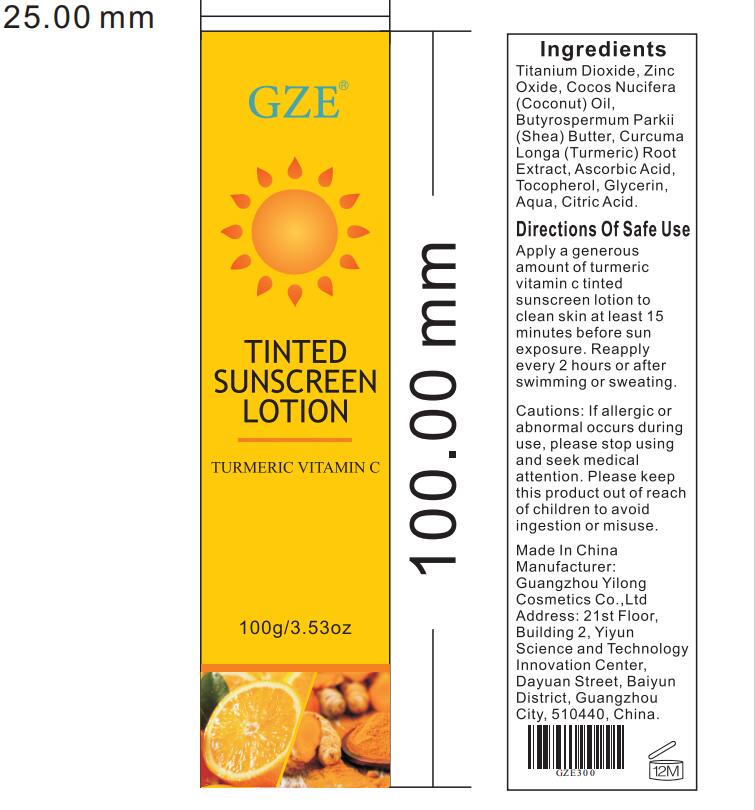 DRUG LABEL: GZE Tinted SunscreenLotion
NDC: 74458-300 | Form: LOTION
Manufacturer: Guangzhou Yilong Cosmetics Co.,Ltd.
Category: otc | Type: HUMAN OTC DRUG LABEL
Date: 20241017

ACTIVE INGREDIENTS: TITANIUM DIOXIDE 7 g/100 g; ZINC OXIDE 7 g/100 g
INACTIVE INGREDIENTS: WATER; SHEA BUTTER; TOCOPHEROL; CITRIC ACID MONOHYDRATE; GLYCERIN; ASCORBIC ACID; TURMERIC; COCONUT OIL

GZE TINTED SUNSCREEN LOTION

ACTIVE INGREDIENT

Titanium Dioxide, Zinc Oxide

INACTIVE INGREDIENT

Cocos Nucifera (Coconut) Oil, Butyrospermum Parkii (Shea) Butter, Curcuma Longa (Turmeric) Root Extract, Ascorbic Acid, Tocopherol, Glycerin, Aqua, Citric Acid.

PURPOSE

Sunscreen.

INDICATIONS AND USAGE

Apply a generous amount of turmeric vitamin c tinted sunscreen lotion to clean skin at least 15 minutes before sun exposure. Reapply every 2 hours or after swimming or sweating.

WARNINGS

For external use only.

Stop use and ask a doctor if rash occurs.

Do not use on damaged or broken skin.

When using this product keep out of eyes. Rinse with water to remove.

Keep out of reach of children. If swallowed, get medical help or contact a Poison Control Center right away.

DOSAGE AND ADMINISTRATION

Apply a generous amount of turmeric vitamin c tinted sunscreen lotion to clean skin at least 15 minutes before sun exposure. Reapply every 2 hours or after swimming or sweating.